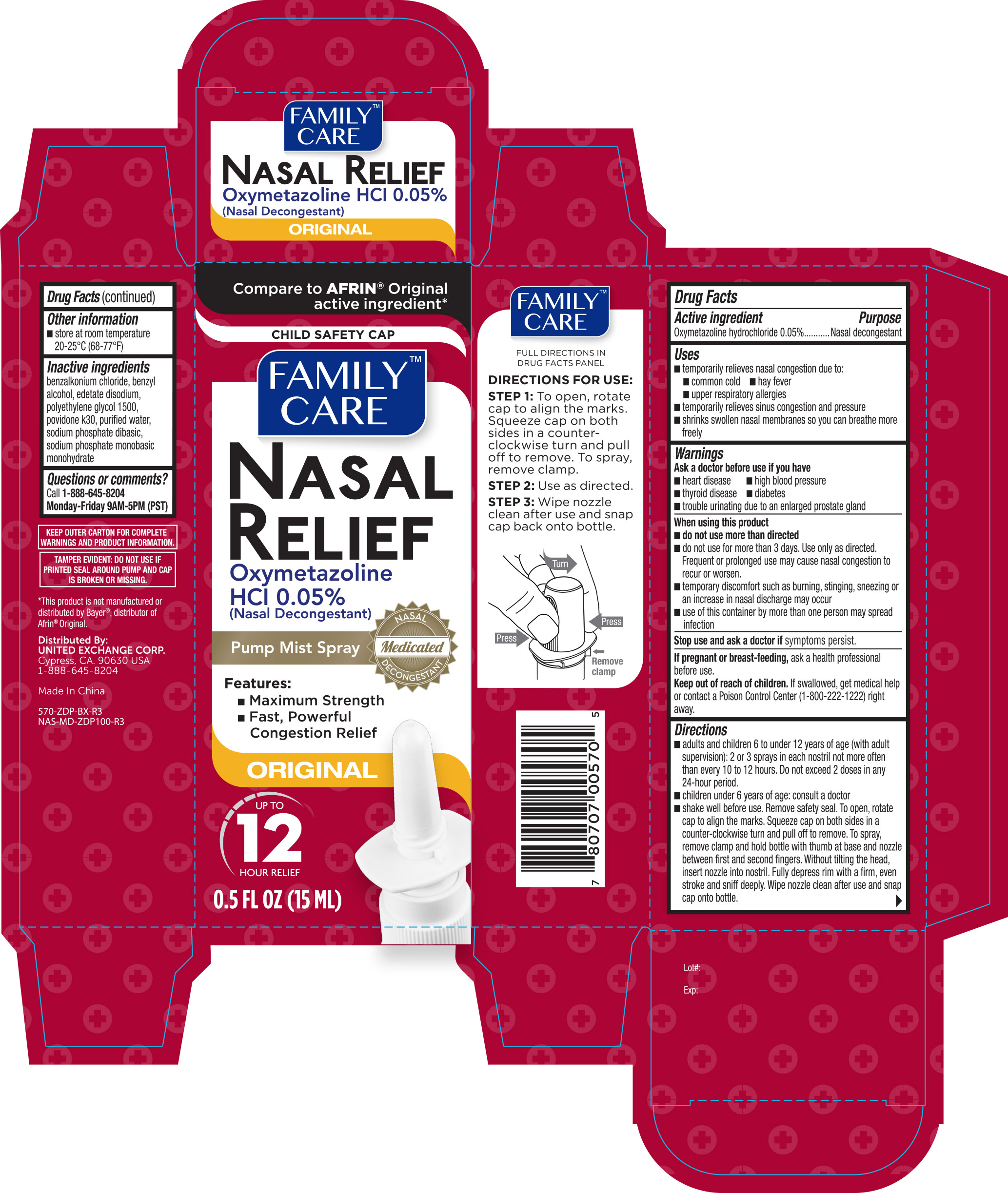 DRUG LABEL: Family Care Nasal Relief
NDC: 65923-570 | Form: SPRAY
Manufacturer: United Exchange Corp
Category: otc | Type: HUMAN OTC DRUG LABEL
Date: 20251028

ACTIVE INGREDIENTS: OXYMETAZOLINE HYDROCHLORIDE 0.05 g/100 mL
INACTIVE INGREDIENTS: WATER; BENZODODECINIUM CHLORIDE; BENZYL ALCOHOL; EDETATE DISODIUM; POLYETHYLENE GLYCOL 1500; POVIDONE K30; SODIUM PHOSPHATE, MONOBASIC, MONOHYDRATE; SODIUM PHOSPHATE, DIBASIC, ANHYDROUS

Family Care Nasal Spray Original 0.5 oz 570 (2018) ZDP

Active ingredient Purpose

Oxymetazoline HCl 0.05%.................................................Nasal Decongestant

Uses

- temporarily relieves nasal congestion due to:
- common cold
- hay fever
- upper respiratory allergies
- shrinks swollen nasal membranes so you can breathe more freely
- temporarily relieves sinus congestion and pressure

Warnings

Ask a doctor before use if you have

- heart disease
- high blood pressure
- thyroid disease
- diabetes
- trouble urinating due to an enlarged prostate gland

When using this product

- do not use more than directed
- do not use for more than 3 days. Use only as directed. Frequent or prolonged use may cause nasal congestion to recur or worsen
- temporary discomfort such as burning, stinging, sneezing or an increase in nasal discharge may occur
- use of this container by more than one person may spread infection

Stop use and ask a doctor if symptoms persist

PREGNANCY OR BREAST FEEDING

If pregnant or breast-feeding, ask a health professional before use

Keep out of reach of children. If swallowed, get medical help or contact a Poison Control Center (1-800-222-1222) right away.

Directions

- adults and children 6 to under 12 years of age (with adult supervision): 2 or 3 sprays in each nostril not more often than every 10 to 12 hours. Do not exceed 2 doses in any 24-hour period.
- children under 6 years of age: consult a doctor. Shake well before use. Remove safety seal. To open, rotate cap to align the marks. Squeeze cap on both sides in a counter-clockwise turn and pull off to remove. To spray, remove clamp and hold bottle with thumb at base and nozzle between first and second fingers. Without tilting the head, insert nozzle into nostril. Fully depress rim with a firm, even stroke and sniff deeply. Wipe nozzle clean after use and snap cap back onto bottle.

Other information

- store between 20° and 25°C (68° and 77°F)
- retain carton for future reference on full labeling

INACTIVE INGREDIENT

Inactive ingredients benzalkonium chloride, benzyl alcohol, edetate disodium, polyethylene glycol 1500, povidone k30, purified water, sodium phosphate dibasic, sodium phosphate monobasic Monohydrate

DOSAGE AND ADMINISTRATION

Distributed By:

United Exchange Corp

Cypress, CA 90630 USA

1-888-645-8204

Made in China